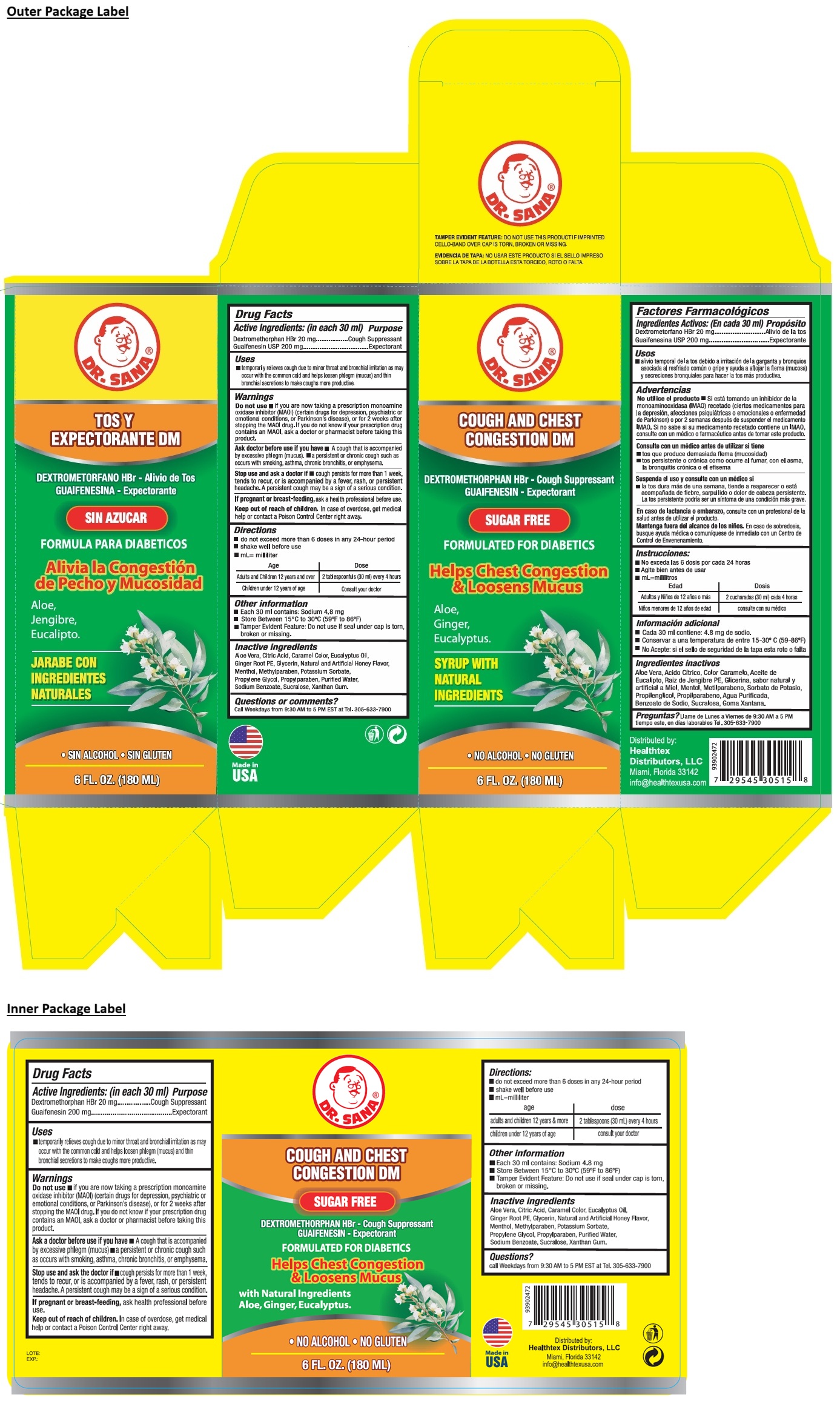 DRUG LABEL: Dr. SANA COUGH AND CHEST CONGESTION DM SUGAR FREE
NDC: 53113-515 | Form: SYRUP
Manufacturer: GADAL Laboratories, Inc
Category: otc | Type: HUMAN OTC DRUG LABEL
Date: 20250723

ACTIVE INGREDIENTS: DEXTROMETHORPHAN HYDROBROMIDE 20 mg/30 mL; GUAIFENESIN 200 mg/30 mL
INACTIVE INGREDIENTS: ALOE VERA LEAF; CITRIC ACID MONOHYDRATE; CARAMEL; EUCALYPTUS OIL; GINGER; GLYCERIN; MENTHOL, UNSPECIFIED FORM; METHYLPARABEN; POTASSIUM SORBATE; PROPYLENE GLYCOL; PROPYLPARABEN; WATER; SODIUM BENZOATE; SUCRALOSE; XANTHAN GUM

Dr. SANA® COUGH AND CHEST CONGESTION DM SUGAR FREE

Active Ingredients: (in each 30 ml)

Dextromethorphan HBr 20 mg
Guaifenesin USP 200 mg

Purpose

Cough Suppressant
Expectorant

Uses

• temporarily relieves cough due to minor throat and bronchial irritation as may occur with the common cold and helps loosen phlegm (mucus) and thin bronchial secretions to make coughs more productive.

Warnings

Do not use • if you are now taking a prescription monoamine oxidase inhibitor (MAOI) (certain drugs for depression, psychiatric or emotional conditions, or Parkinson's disease), or for 2 weeks after stopping the MAOI drug. If you do not know if your prescription drug contains an MAOI, ask a doctor or pharmacist before taking this product.

Ask a doctor before use if you have • A cough that is accompanied by excessive phlegm (mucus) • a persistent or chronic cough such as occurs with smoking, asthma, chronic bronchitis, or emphysema.

Stop use and ask the doctor if • cough persists for more than 1 week, tends to recur, or is accompanied by a fever, rash, or persistent headache. A persistent cough may be a sign of a serious condition.

If pregnant or breast-feeding, ask health professional before use.

Keep out of reach of children. In case of overdose, get medical help or contact a Poison Control Center right away.

Directions:

• do not exceed more than 6 doses in any 24-hour period
• shake well before use
• mL=milliliter

age | dose
adults and children 12 years & more | 2 tablespoons (30 mL) every 4 hours
children under 12 years of age | consult your doctor

Other information

• Each 30 ml contains: Sodium 4.8 mg
• Store Between 15°C to 30°C (59°F to 86°F)
• Tamper Evident Feature: Do not use if seal under cap is torn, broken or missing.

Inactive ingredients

Aloe Vera, Citric Acid, Caramel Color, Eucalyptus Oil, Ginger Root PE, Glycerin, Natural and Artificial Honey Flavor, Menthol, Methylparaben, Potassium Sorbate, Propylene Glycol, Propylparaben, Purified Water, Sodium Benzoate, Sucralose, Xanthan Gum.

Questions?

call Weekdays from 9:30 AM to 5 PM EST at Tel. 305-633-7900

FORMULATED FOR DIABETICS

Helps Chest Congestion & Loosens Mucus

Aloe,
Ginger,
Eucalyptus.

SYRUP WITH
NATURAL
INGREDIENTS

• NO ALCOHOL • NO GLUTEN

Distributed by:
Healthtex Distributors, LLC
Miami, Florida 33142
info@healthtexusa.com

Made in USA

TAMPER EVIDENT FEATURE: DO NOT USE THIS PRODUCT IF IMPRINTED CELLO-BAND OVER CAP IS TORN, BROKEN OR MISSING.